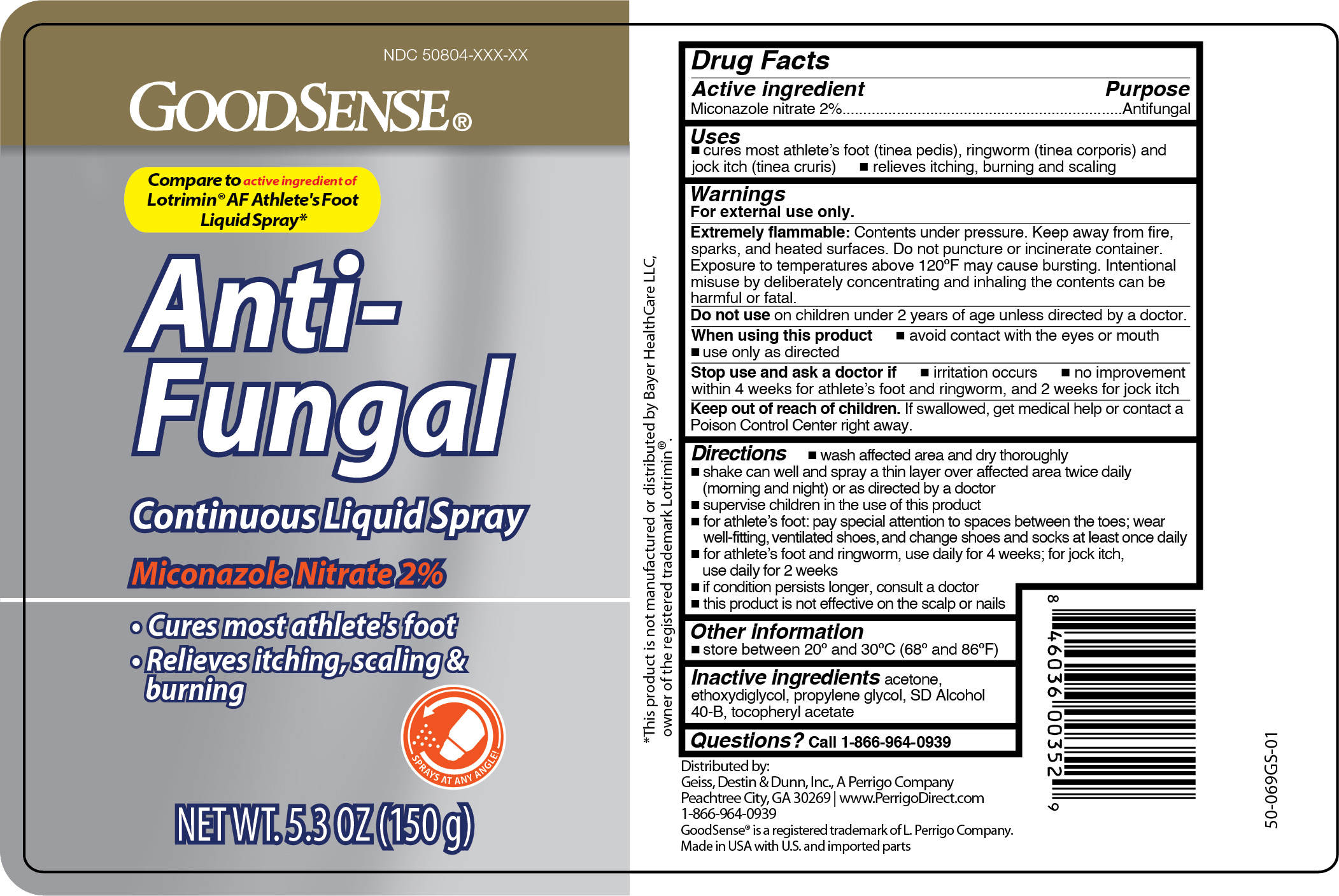 DRUG LABEL: Miconazole nitrate
NDC: 50804-136 | Form: AEROSOL, SPRAY
Manufacturer: GEISS, DESTIN AND DUNN, INC.
Category: otc | Type: HUMAN OTC DRUG LABEL
Date: 20251030

ACTIVE INGREDIENTS: MICONAZOLE NITRATE 3 g/150 g
INACTIVE INGREDIENTS: ACETONE; DIETHYLENE GLYCOL MONOETHYL ETHER; PROPYLENE GLYCOL; ALCOHOL; .ALPHA.-TOCOPHEROL ACETATE

GoodSense Antifungal Miconazole Liquid Continuous Spray

Active ingredient

Miconazole nitrate 2%

Purpose

Antifungal

Uses

- cures most athlete's foot (linea pedis), ringworm (linea corporis) and jock itch (linea cruris)
- relieves itching, burning and scaling

Warnings

For external use only.

Extremely flammable:

Contents under pressure. Keep away from fire, sparks, and heated surfaces. Do not puncture or incinerate container. Exposure to temperatures above 120ºF may cause burning, intentional misuse by deliberately concentrating and inhaling the contents can be harmful or fatal.

Do not use

on children under 2 years of age unless directed by a doctor

When using this product

- avoid contact with the eyes or mouth
- use only as directed

Stop use and ask a doctor if

- irritation occurs
- no improvement within 4 weeks for athlete's foot and ringworm, and 2 weeks for jock itch

Keep out of reach of children.

If swallowed, get medical help or contact a Poison Control Center right away.

Directions

- wash affected area and dry thoroughly
- shake can well and spray a thin layer over affected area twice daily (morning and night) or as directed by a doctor
- supervise children in the use of this product
- for athlete's foot: pay special attention to spaces between the toes; wear well-fitting, ventilated shoes, and change shoes and socks at least once daily
- for athlete's foot and ringworm, use daily for 4 weeks; for jock itch, use daily for 2 weeks
- if conditions persists longer, consult a doctor
- this product is not effective on the scalp or nails

Other information

store between 20º and 30ºC (68º and 86ºF)

Inactive ingredients

acetone, ethoxdiyglycol, propylene glycol, SD alcohol 40-B, tocopheryl acetate

Questions?

Call 1-866-964-0939

Principal Display Panel

GOODSENSE

Anti-

Fungal

Continuous Liquid Spray

Miconazole Nitrate 2%

Liquid Countinuous Spray

- Cures most athlete's foot
- Relieves itching, scaling & burning

NET WT. 5.3 OZ (150g)